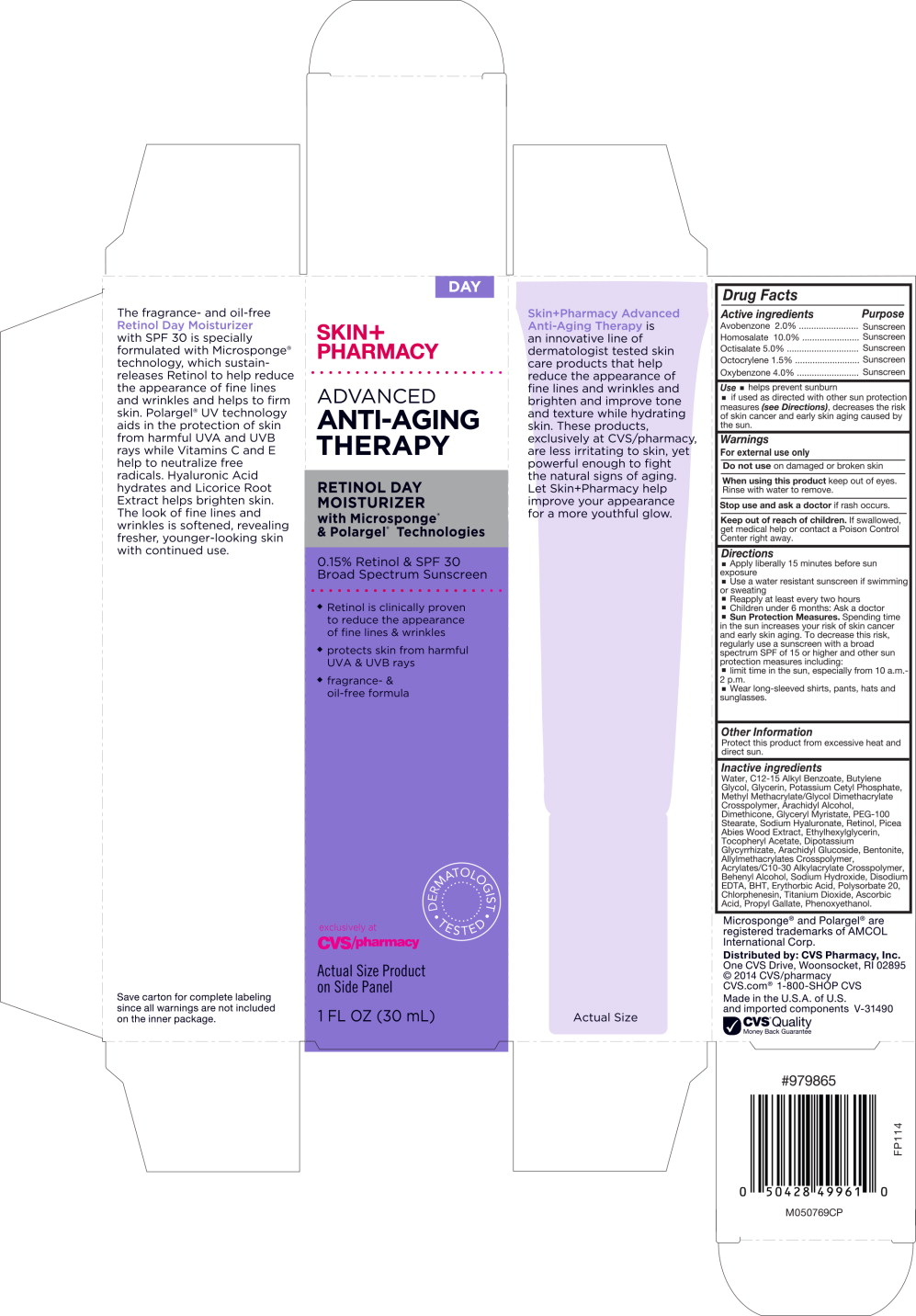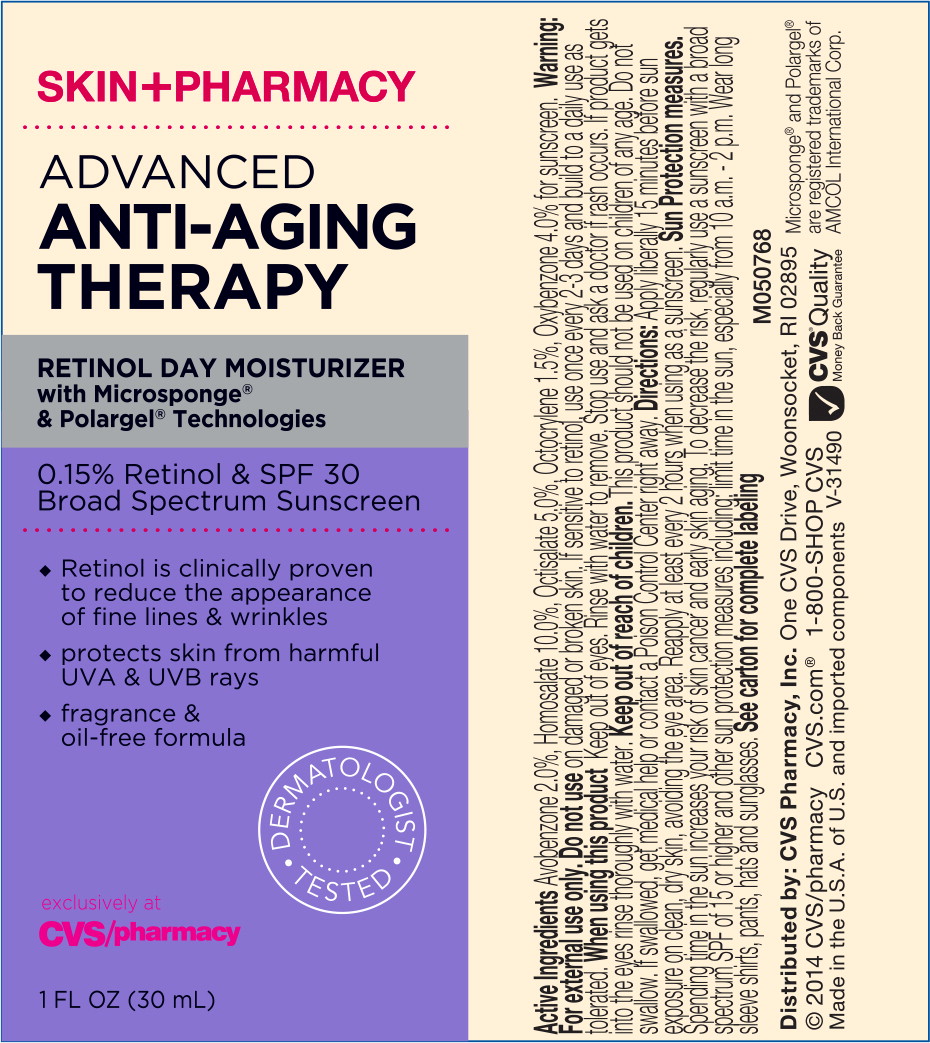 DRUG LABEL: SkinPharmacy Advanced Anti-Aging Therapy Retinol Day Moisturizer SPF 30
NDC: 69842-022 | Form: LIQUID
Manufacturer: CVS Health
Category: otc | Type: HUMAN OTC DRUG LABEL
Date: 20170307

ACTIVE INGREDIENTS: homosalate 100 mg/1 mL; octisalate 50 mg/1 mL; avobenzone 20 mg/1 mL; octocrylene 15 mg/1 mL; oxybenzone 40 mg/1 mL
INACTIVE INGREDIENTS: water; butylene glycol; polyethylene glycol 400; high density polyethylene; dimethicone; tetrapeptide-21; hexyldecanol; picea abies wood; rapeseed sterol; aloe vera leaf; sodium ascorbyl phosphate; cetylhydroxyproline palmitamide; wheat germ; glycerin; levomenol; tocopherol; vitamin a palmitate; .alpha.-tocopherol acetate, DL-; sodium polyacrylate (8000 mw); carbomer copolymer type A; lauryl glucoside; titanium dioxide; bentonite; stearic acid; edetate disodium; ethylhexylglycerin; phenoxyethanol; chlorphenesin

Drug Facts

Active ingredients

Avobenzone 2.0%

Homosalate 10.0%

Octisalate 5.0%

Octocrylene 1.5%

Oxybenzone 4.0%

Purpose

Sunscreen

Sunscreen

Sunscreen

Sunscreen

Sunscreen

Uses

- Helps prevent sunburn
- If used as directed with other sun protection measures (see Directions), decreases the risk of skin cancer and early skin aging cause by the sun.

Warnings

For external use only.

Do not use on damaged or broken skin

When using this product keep out of eyes. Rinse with water to remove.

Stop use and ask a doctor if rash occurs.

Keep out of reach of children. If swallowed, get medical help or contact a Poison Control Center right away.

Directions

- Apply liberally 15 minutes before sun exposure
- Use a water resistant sunscreen if swimming or sweating
- Reapply at least every 2 hours
- Children under 6 months: Ask a doctor
- Sun Protection Measures. Spending time in the sun increases your risk of skin cancer and early skin aging. To decrease this risk, regularly use a sunscreen with a Broad Spectrum SPF value of 15 or higher and other sun protection measures including:
- limit time in the sun, especially from 10 a.m.-2 p.m.
- -wear long-sleeved shirts, pants, hats and sunglasses

Other information

Protect this product from excessive heat and direct sun.

Inactive ingredients

Water, C12-15 Alkyl Benzoate, Butylene Glycol, Glycerin, Potassium Cetyl Phosphate, Methyl Methacrylate/Glycol Dimethacrylate Crosspolymer, Arachidyl Alcohol, Dimethicone, Glyceryl Myristate, PEG-100 Stearate, Sodium Hyaluronate, Retinol, Picea Abies Wood Extract, Ethylhexylglycerin, Tocopherol Acetate, Dipotassium Glycyrrhizate, Arachidyl Glucoside, Bentonite, Allylmethacrylates Crosspolymer, Acrylates/C10-30 Alkylacrylate Crosspolymer, Behenyl Alcohol, Sodium Hydroxide, Disodium EDTA, BHT, Erythorbic Acid, Polysorbate 20, Chlorphenesin, Titanium Dioxide, Ascorbic Acid, Propyl Gallate, Phenoxyethanol.

Microsponge® and Polargel® are registered trademarks of AMCOL International Corp.

Distributed by: CVS Pharmacy, Inc.
One CVS Drive, Woonsocket, RI 02895
© 2014 CVS/pharmacy
CVS.com® 1-800-SHOP CVS

Made in the U.S.A. of U.S. and imported components V-31490

CVS® Quality
Money Back Guarantee

Principal Display Panel - Carton Label

DAY

SKIN+
PHARMACY

ADVANCED
ANTI-AGING
THERAPY

RETINOL DAY
MOISTURIZER
with Microsponge®
& Polargel® Technologies

0.15% Retinol & SPF 30
Broad Spectrum Screen

♦ Retinol is clinically proven
  to reduce the appearance
  of fine lines & wrinkles
♦ protects skin from harmful
  UVA & UVB rays
♦ fragrance- &
  oil-free formula

exclusively at
CVS/pharmacy

DERMATOLOGIST TESTED

Actual Size Product on Side Panel

1 FL OZ (30 mL)

Principal Display Panel - Tube Label

SKIN+PHARMACY

ADVANCED
ANTI-AGING
THERAPY

RETINOL DAY MOISTURIZER
with Microsponge®
& Polargel® Technologies

0.15% Retinol & SPF 30
Broad Spectrum Screen

♦ Retinol is clinically proven to reduce the appearance of fine lines & wrinkles
♦ protects skin from harmful UVA & UVB rays
♦ fragrance- & oil-free formula

exclusively at
CVS/pharmacy

DERMATOLOGIST TESTED

1 FL OZ (30 mL)